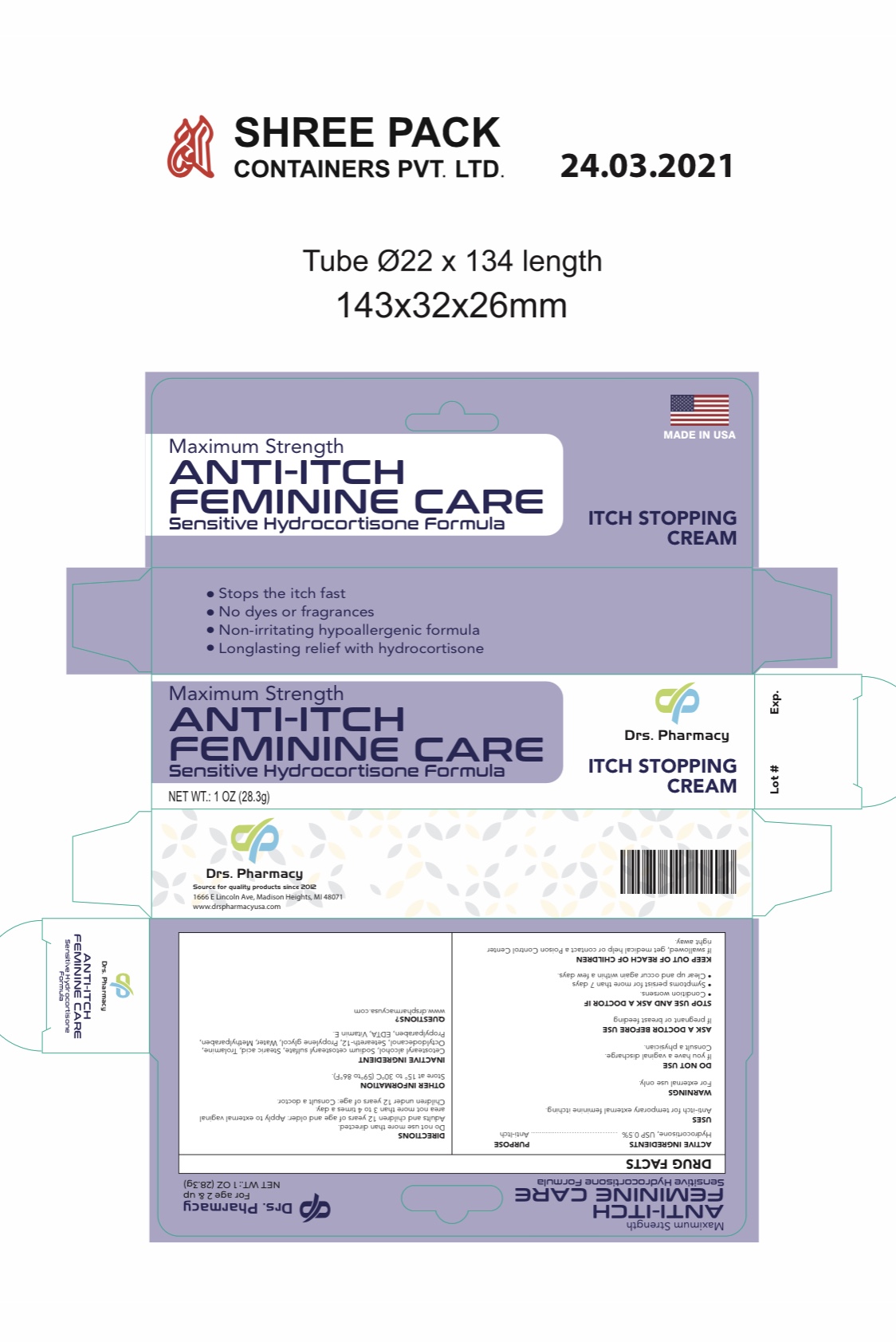 DRUG LABEL: ANTI-ITCH FEMININE CARE
NDC: 80489-103 | Form: CREAM
Manufacturer: OL PHARMA TECH, LLC Drs PHARMACY
Category: otc | Type: HUMAN OTC DRUG LABEL
Date: 20250109

ACTIVE INGREDIENTS: HYDROCORTISONE 5 mg/1 g
INACTIVE INGREDIENTS: PROPYLENE GLYCOL; PROPYLPARABEN; .ALPHA.-TOCOPHEROL; METHYLPARABEN; EDETATE DISODIUM; CETEARETH-12; WATER; STEARIC ACID; SODIUM CETOSTEARYL SULFATE; CETOSTEARYL ALCOHOL; OCTYLDODECANOL; TROLAMINE

ACTIVE INGREDIENT

Hydrocortisone, USP 0.5%

PURPOSE

Anti-itch

USES

For temporary external feminine itching

WARNINGS

For External Use Only

Avoid Contact with eyes

DIRETIONS

Adults and children 12 years and older Apply to external vaginal area not more than 3 to 4 times a day
Children under 12 years Consult a doctor

Stop use and ask a doctor if

- you have a vaginal discharge. Consult a physician.
- condition worsens, or if symptoms persist for more than 7 days, or clear up and occur again in a few days.

KEEP OUT OF REACH OF CHILDREN

If swallowed, get medical help or contact a Poison Control Center right away.

OTHER INFORMATION

- store at 20°-25°C (68°-77°F)

INACTIVE INGREDIENT

cetostearyl alcohol, sodium cetostearyl sulfate, stearic acid, trolamine, decyl oleate, propylene glycol, water, methyl paraben, propyl paraben, EDTA, vitamin E

QUESTIONS

www.drspharmacyusa.com